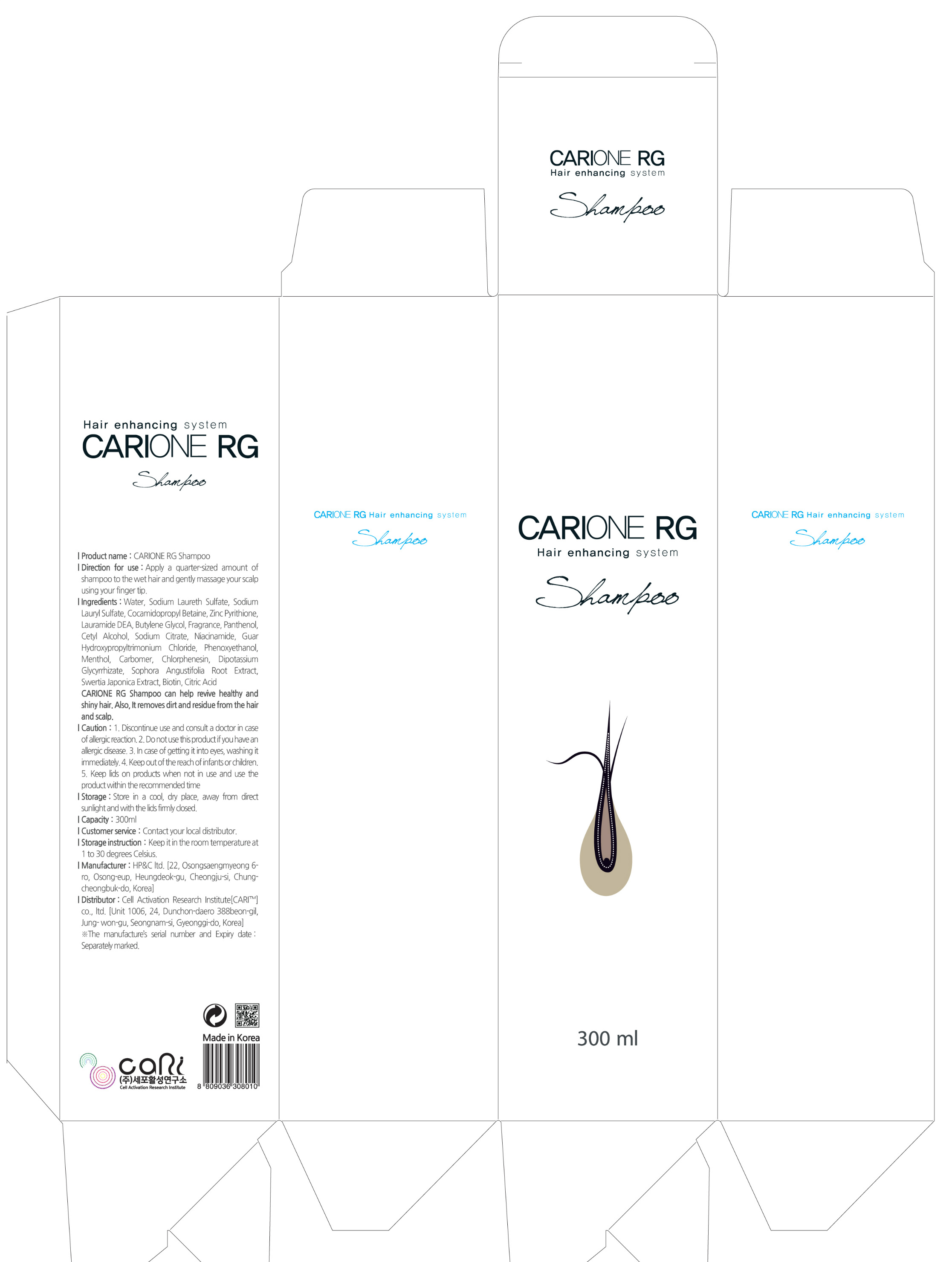 DRUG LABEL: CARIONE RG TONER
NDC: 71039-0002 | Form: LIQUID
Manufacturer: Cell Activation Research Institute Co., Ltd
Category: otc | Type: HUMAN OTC DRUG LABEL
Date: 20161023

ACTIVE INGREDIENTS: MENTHOL 0.3 g/100 mL; SALICYLIC ACID 0.25 g/100 mL
INACTIVE INGREDIENTS: WATER; PANTHENOL

Drug Facts

ACTIVE INGREDIENT

Sailcylic Acid

INACTIVE INGREDIENT

Phellinus linteus grown on germinated brown rice (PBR), Sophora Angustifolia Root Extract, Swertia Japonica Extract, Bambusa Vulgaris Extract, Ficus Carica (Fig) Fruit Extract, Menthol, Panthenol, etc.

PURPOSE

For hair and scalp care

keep out or reach of the children

INDICATIONS AND USAGE

Spray onto the scalp directly and then massage gently until completely absorbed, after using shampoo.

Recommend to use it once or twice a day.

Do not use a hair dryer after spraying.

It is okay to use a hair dryer before spraying.

WARNINGS

1. Discontinue use and consult a doctor in case of allergic reaction.
2. Do not use this product if you have an allergic disease.
3. In case of getting it into eyes, washing it immediately.
4. Keep out of the reach of infants or children.
5. Keep lids on products when not in use and use the product wihin the recommended time.

Storage: Store in a cool, dry place, away from direct sunlight and with the lids firmly close.

DOSAGE AND ADMINISTRATION

For external use only